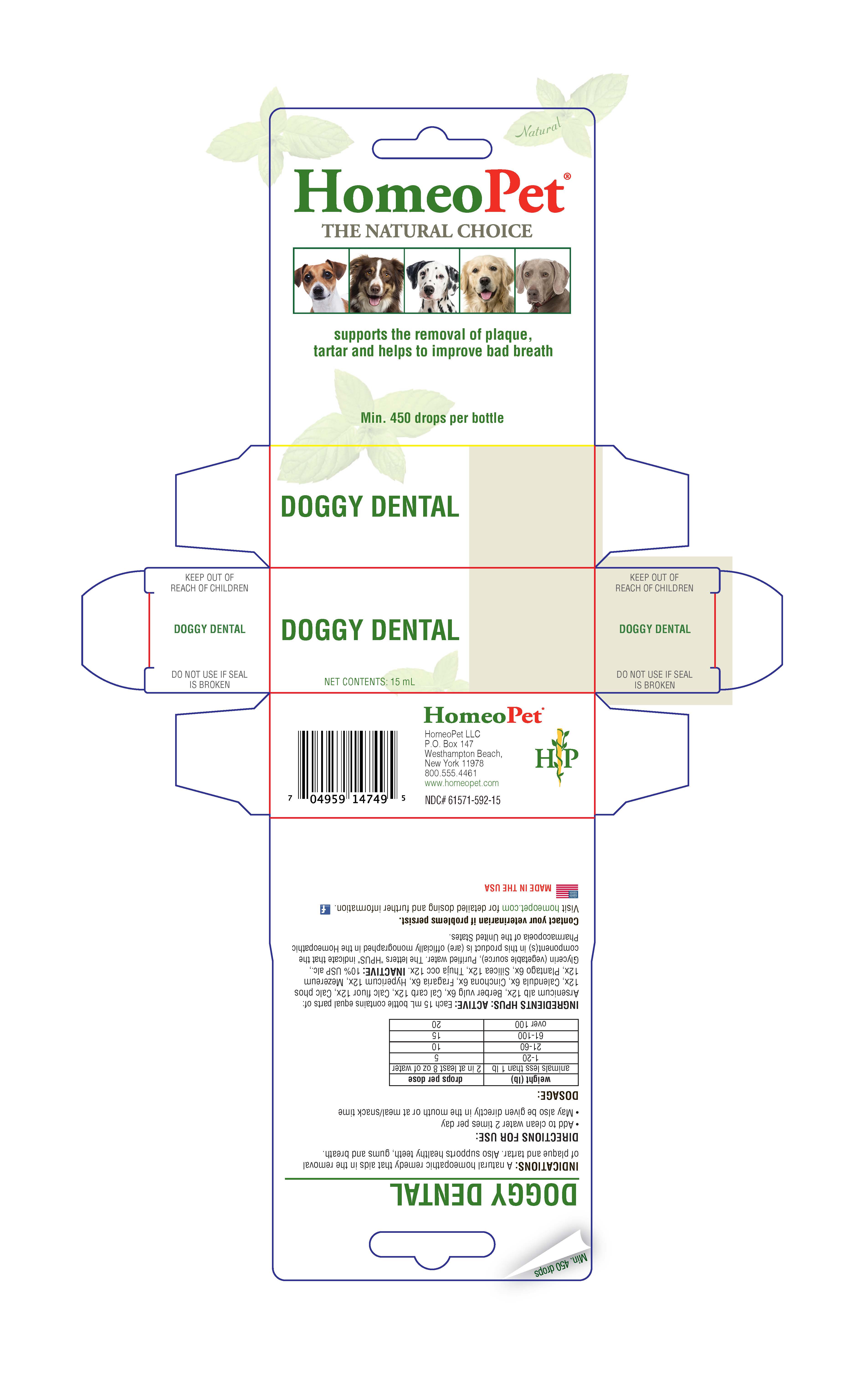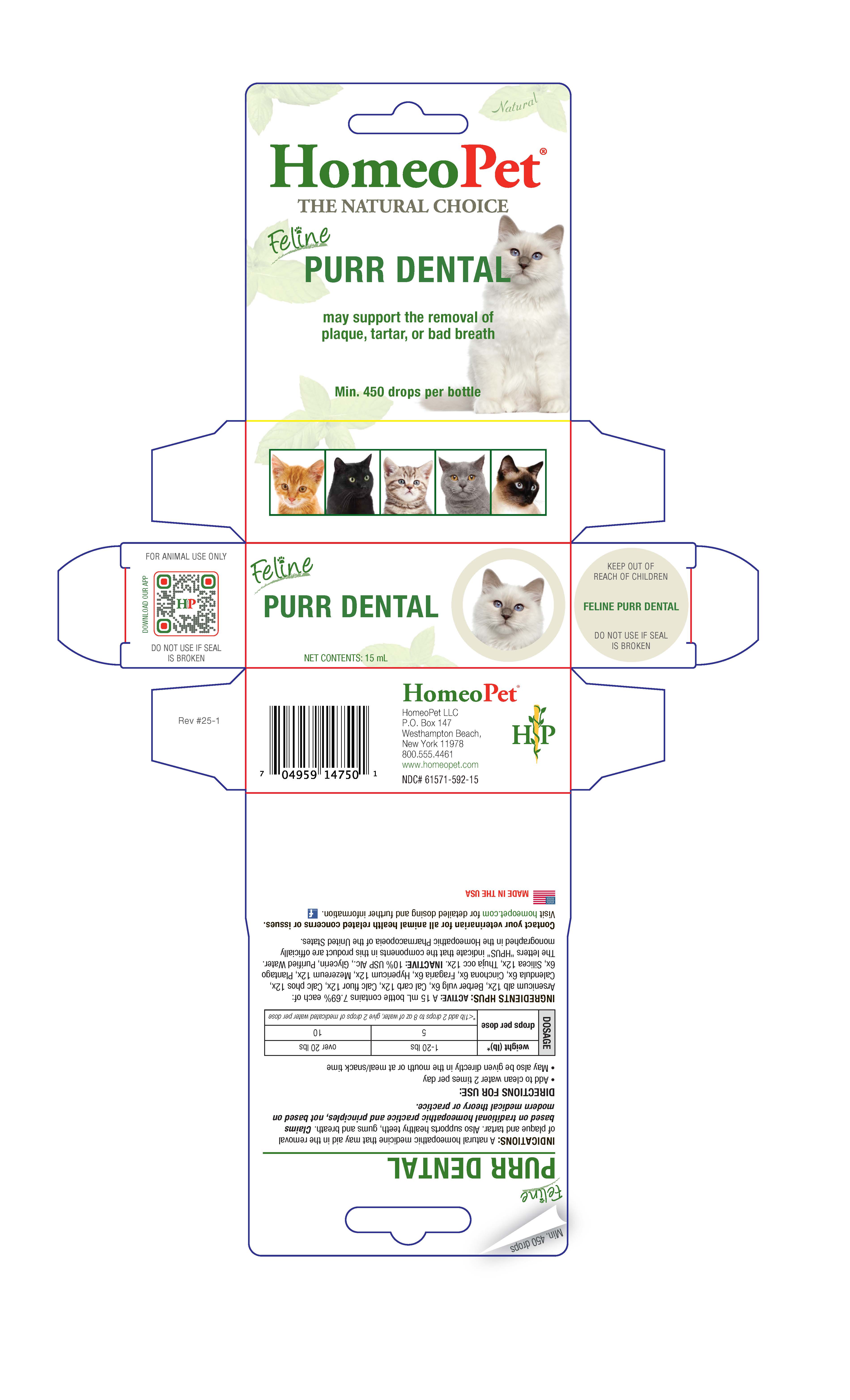 DRUG LABEL: Doggy Dental, Purr Dental
NDC: 61571-592 | Form: LIQUID
Manufacturer: HomeoPet, LLC
Category: homeopathic | Type: OTC ANIMAL DRUG LABEL
Date: 20251216

ACTIVE INGREDIENTS: ARSENIC TRIOXIDE 12 [hp_X]/15 mL; BERBERIS VULGARIS ROOT BARK 6 [hp_X]/15 mL; OYSTER SHELL CALCIUM CARBONATE, CRUDE 12 [hp_X]/15 mL; CALCIUM FLUORIDE 12 [hp_X]/15 mL; TRIBASIC CALCIUM PHOSPHATE 12 [hp_X]/15 mL; CALENDULA OFFICINALIS FLOWERING TOP 6 [hp_X]/15 mL; CINCHONA OFFICINALIS BARK 6 [hp_X]/15 mL; ALPINE STRAWBERRY 6 [hp_X]/15 mL; HYPERICUM PERFORATUM 12 [hp_X]/15 mL; DAPHNE MEZEREUM BARK 12 [hp_X]/15 mL; PLANTAGO MAJOR 6 [hp_X]/15 mL; SILICON DIOXIDE 12 [hp_X]/15 mL; THUJA OCCIDENTALIS LEAFY TWIG 12 [hp_X]/15 mL
INACTIVE INGREDIENTS: ALCOHOL; GLYCERIN; WATER

Doggy Dental, Purr Dental

Doggy Dental Purr Dental

may support the removal of plaque, tartar, or bad breath

INDICATIONS

A natural homeopathic medicine that may aid in the removal of plaque and tartar. Also supports healthy, teeth, gums and breath. Claims based on traditional homeopathic practice and principles, not based on modern medical theory or practice.

ACTIVE INGREDIENT

INGREDIENTS HPUS: ACTIVE: Arsenicum alb 12x, Berber vulg 6x, Cal carb 12x, Cal fluor 12x, Calc phos 12x, Calendula 6x, Cinchona 6x, Fragaria 6x, Hypericum 12x, Mezereum 12x, Plantago 6x, Silicea 12x, Thuja occ 12x.

INACTIVE: UPS alc., Glycerin, Purified water.

ASK DOCTOR

Contact your veterinarian for all animal health related concerns or issues.

Visit homeopet.com for detailed dosing and further information.

DOSAGE
weight (lb)* | 1-20 lbs | over 20 lbs
drops per dose | 5 | 10
drops per dose | *<1 lb add 2 drops to 8 oz of water, give 2 drops of medicated water per dose